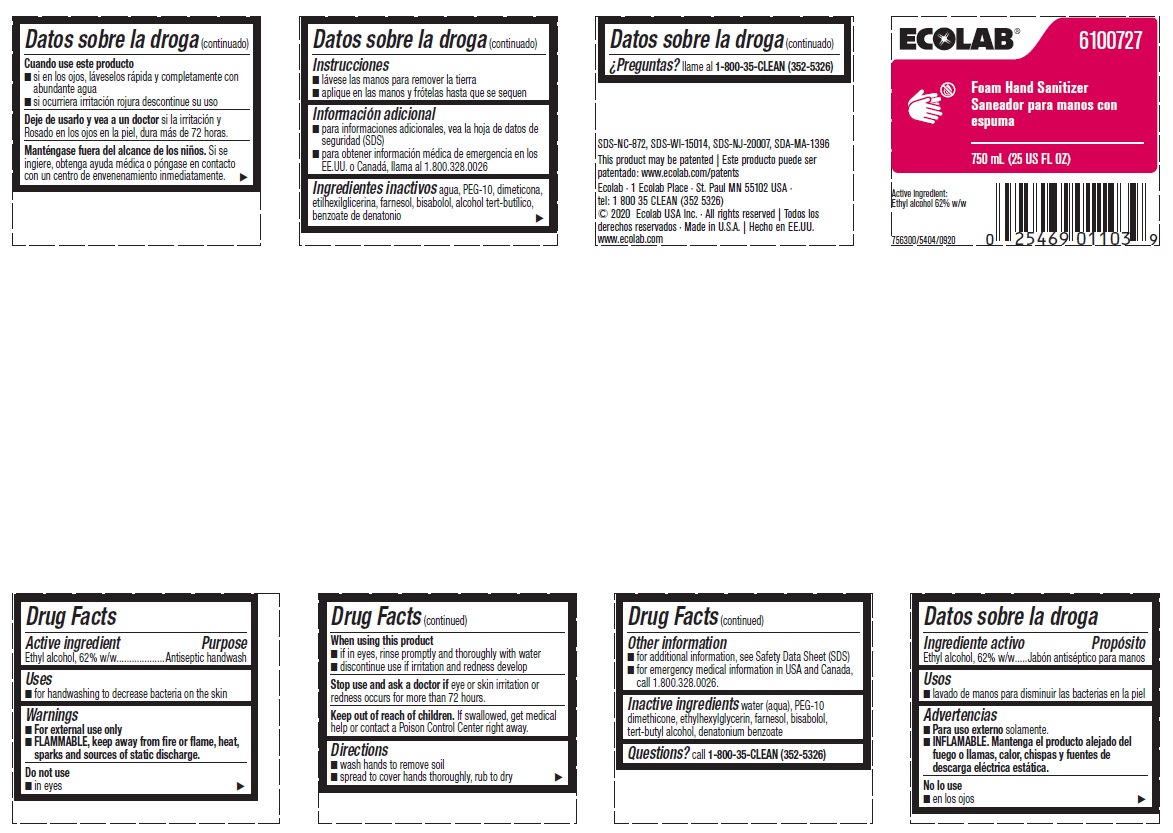 DRUG LABEL: Ecolab
NDC: 47593-472 | Form: SOLUTION
Manufacturer: Ecolab Inc.
Category: otc | Type: HUMAN OTC DRUG LABEL
Date: 20251216

ACTIVE INGREDIENTS: ALCOHOL 62 mL/100 mL
INACTIVE INGREDIENTS: WATER; PEG-10 DIMETHICONE (600 CST); ETHYLHEXYLGLYCERIN; FARNESOL; LEVOMENOL; TERT-BUTYL ALCOHOL; DENATONIUM BENZOATE

Drug Facts

Active ingredient

Ethyl alcohol, 62% w/w

Purpose

Antiseptic handwash

Uses

- for hand washing to decrease bacteria on the skin

Warnings

- For external use only
- FLAMMABLE, keep away from fire or flame, heat, sparks and sources of static discharge.

Do not use

- in eyes

When using this product

- if in eyes, rinse promptly and throughly with water
- discontinue use if irritation and redness develop

Stop use and ask doctor if skin irritation and redness persists from more than 72 hours

Keep out of reach of children. If swallowed, get medical help or contact a Poison Control Center right away.

Directions

- wash hands to remove soil
- spread to cover hands thoroughly, rub to dry

Other information

- for additional information, see Safety Data Sheet (SDS)
- for emergency medical information in USA and Canada, call 1.800.328.0026

INACTIVE INGREDIENT

Inactive ingredients water (aqua), PEG-10 dimethicone, ethylhexylglycerin, farnesol, bisabolol, tert-butyl alcohol, denatonium benzoate

Questions? call 1-800-35-CLEAN (352-5326)

Principal display panel and representative label

ECOLAB® 6100727

Foam Hand Sanitizer

750 ML (25 US FL OZ)

Active Ingredient:

Ethyl aclohol, 62% w/w

756300/5404/0920

SDS-NC-872, SDS-WI-15014, SDS-NJ-20007, SDA-MA-1396

This product may be patented | Este producto puede ser

patentado: www.ecolab.com/patents

Ecolab · 1 Ecolab Place · St. Paul MN 55102 USA ·

tel: 1 800 35 CLEAN (352 5326)

© 2020 Ecolab USA Inc. · All rights reserved | Todos los derechos reservados · Made in U.S.A. | Hecho en EE.UU. www.ecolab.com